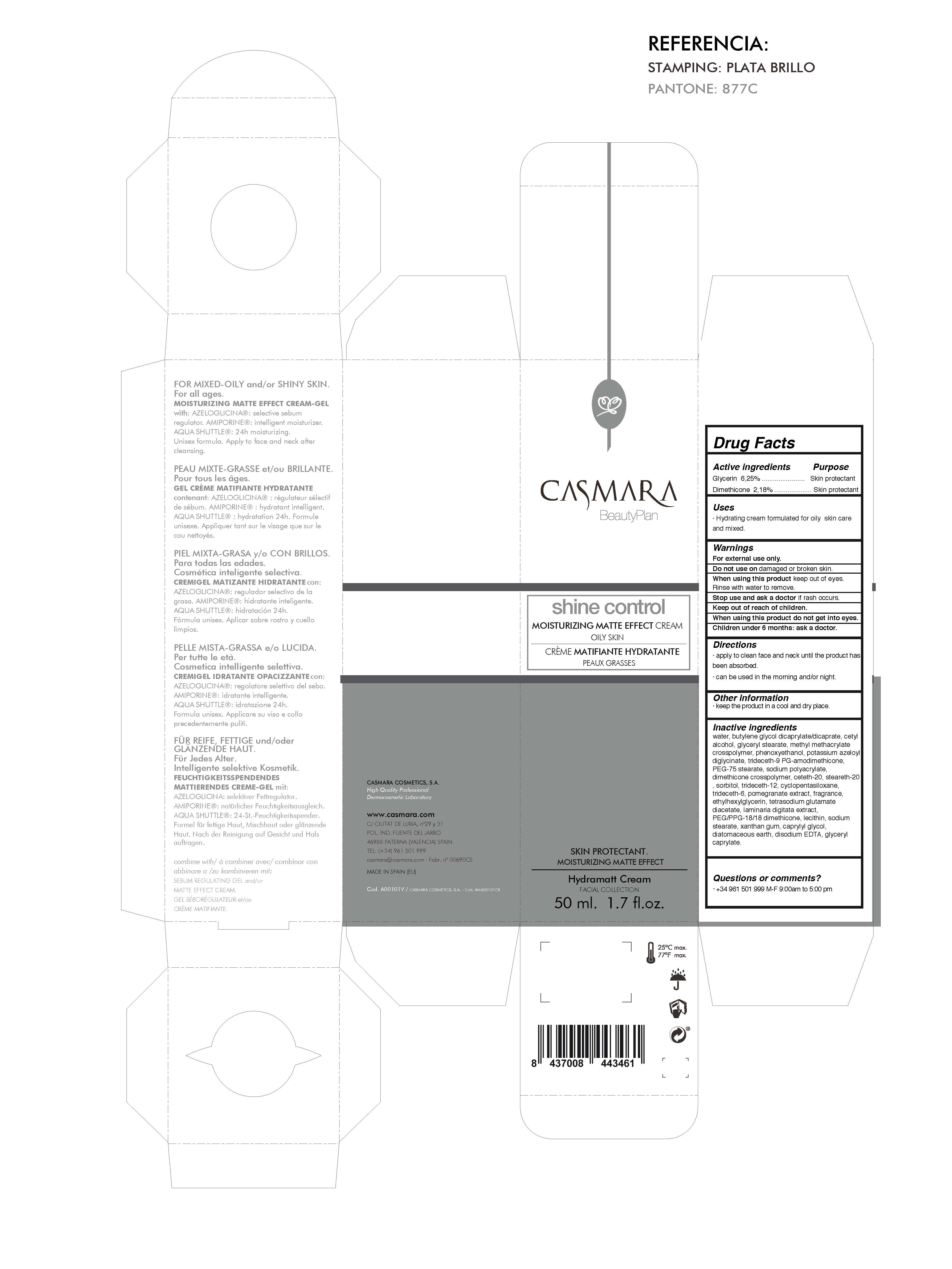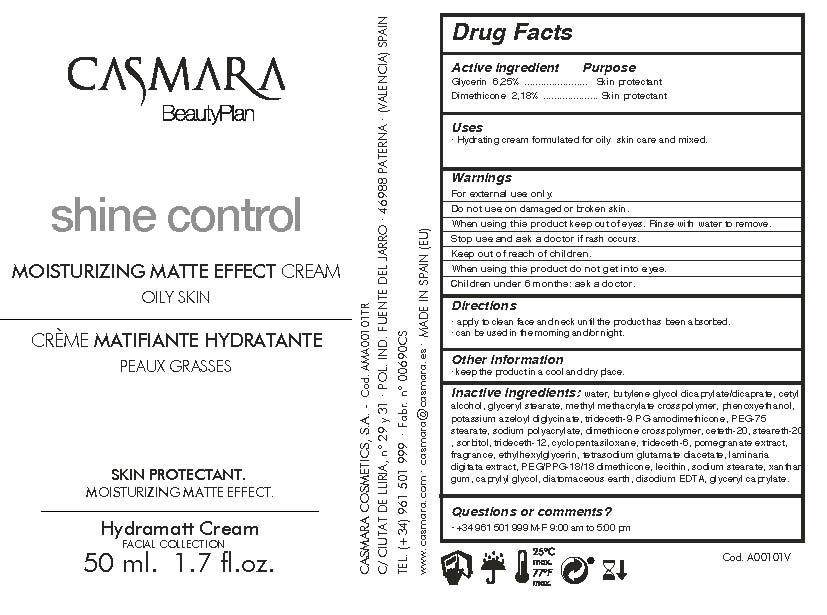 DRUG LABEL: Shine Control Moisturizing Matte Effect Cream
NDC: 20151-097 | Form: CREAM
Manufacturer: CASMARA COSMETICS, SA
Category: otc | Type: HUMAN OTC DRUG LABEL
Date: 20170302

ACTIVE INGREDIENTS: GLYCERIN 6.25 mg/1 mL; DIMETHICONE 2.18 mg/1 mL
INACTIVE INGREDIENTS: SORBITOL 0.25 mg/1 mL; SODIUM POLYACRYLATE (2500000 MW) 0.5 mg/1 mL; SILANAMINE 0.85 mg/1 mL; DIMETHICONE CROSSPOLYMER (450000 MPA.S AT 12% IN CYCLOPENTASILOXANE) 0.32 mg/1 mL; DIATOMACEOUS EARTH 0.01 mg/1 mL; TRIDECETH-12 0.15 mg/1 mL; BUTYLENE GLYCOL DICAPRYLATE/DICAPRATE 6 mg/1 mL; CYCLOMETHICONE 5 0.15 mg/1 mL; WATER 75.93 mg/1 mL; CETYL ALCOHOL 1.31 mg/1 mL; GLYCERYL STEARATE SE 1.31 mg/1 mL; METHYL METHACRYLATE/GLYCOL DIMETHACRYLATE CROSSPOLYMER 1 mg/1 mL; PEG-75 STEARATE 0.61 mg/1 mL; XANTHAN GUM 0.025 mg/1 mL; CETETH-20 0.2 mg/1 mL; STEARETH-20 0.26 mg/1 mL; ETHYLHEXYLGLYCERIN 0.1 mg/1 mL; TETRASODIUM GLUTAMATE DIACETATE 0.094 mg/1 mL; LAMINARIA DIGITATA 0.075 mg/1 mL; PHENOXYETHANOL 0.92 mg/1 mL; HYDROGENATED SOYBEAN LECITHIN 0.05 mg/1 mL; POMEGRANATE 0.1 mg/1 mL; POTASSIUM AZELOYL DIGLYCINATE 0.9 mg/1 mL; PEG/PPG-18/18 DIMETHICONE 0.06 mg/1 mL; SODIUM STEARATE 0.03 mg/1 mL; CAPRYLYL GLYCOL 0.02 mg/1 mL; TRIDECETH-6 0.15 mg/1 mL; EDETATE DISODIUM 0.007 mg/1 mL; GLYCERYL MONOCAPRYLATE 0.0025 mg/1 mL

Shine Control
Moisturizing Matte Effect Cream
Oily Skin

Active Ingredients Purpose

Glycerin 6.25%.................... Skin Protectant

Dimethicone 2.18%................Skin Protectant

Uses

. Hydrating cream formulated for oily skin care and mixed

Uses

- Hydrating cream formulated for oily skin care and mixed

Warnings

For external use only.

Do not use on damaged or broken skin.

When using this product keep our of the eyes. Rinse with water to remove.

Stop use and ask a doctor if rash occurs.

Keep out of reach of children.

Whhen using this product do not get into eyes.

Children under 6 months: as a doctor.

Keep out of reach of children.

Warnings

Stop use and ask a doctor if rash occurs.

Questions or comments?

(305) 777-0548 M-F 9:00 am to 5:00 pm

Directions

. apply to clean face and neck until the product has been absorbed

. can be used in the morning and/or night.

Other information

. keep the product in a cool and dry place.

Inactive ingredients

Water, Butylene glycol dicaprylate/dicaprate, Cetyl alcohol, Glyceryl stearate, Methyl methacrylate crosspolymer, Phenoxyethanol
Potassium azeloyl diglycinate, Trideceth-9 PG-Amodimethicone , PEG-75 stearate, Sodium Polyacrylate , Dimethicone crosspolymer, Ceteth-20, Steareth-20, Sorbitol, Trideceth-12, Cyclopentasiloxane, Trideceth-6, Pomegranate extract, Fragrance
Ethylhexylglycerin, Tetrasodium glutamate diacetate, Laminaria digitata extract, PEG/PPG-18/18 dimethicone, Lecithin , Sodium stearate, Xanthan gum, Caprylyl glycol, Diatomaceous Earth, Disodium EDTA , Glyceryl caprylate

Directions

. apply to clean face and neck until the product has been absorbed

. can be used in the morning and/or night.